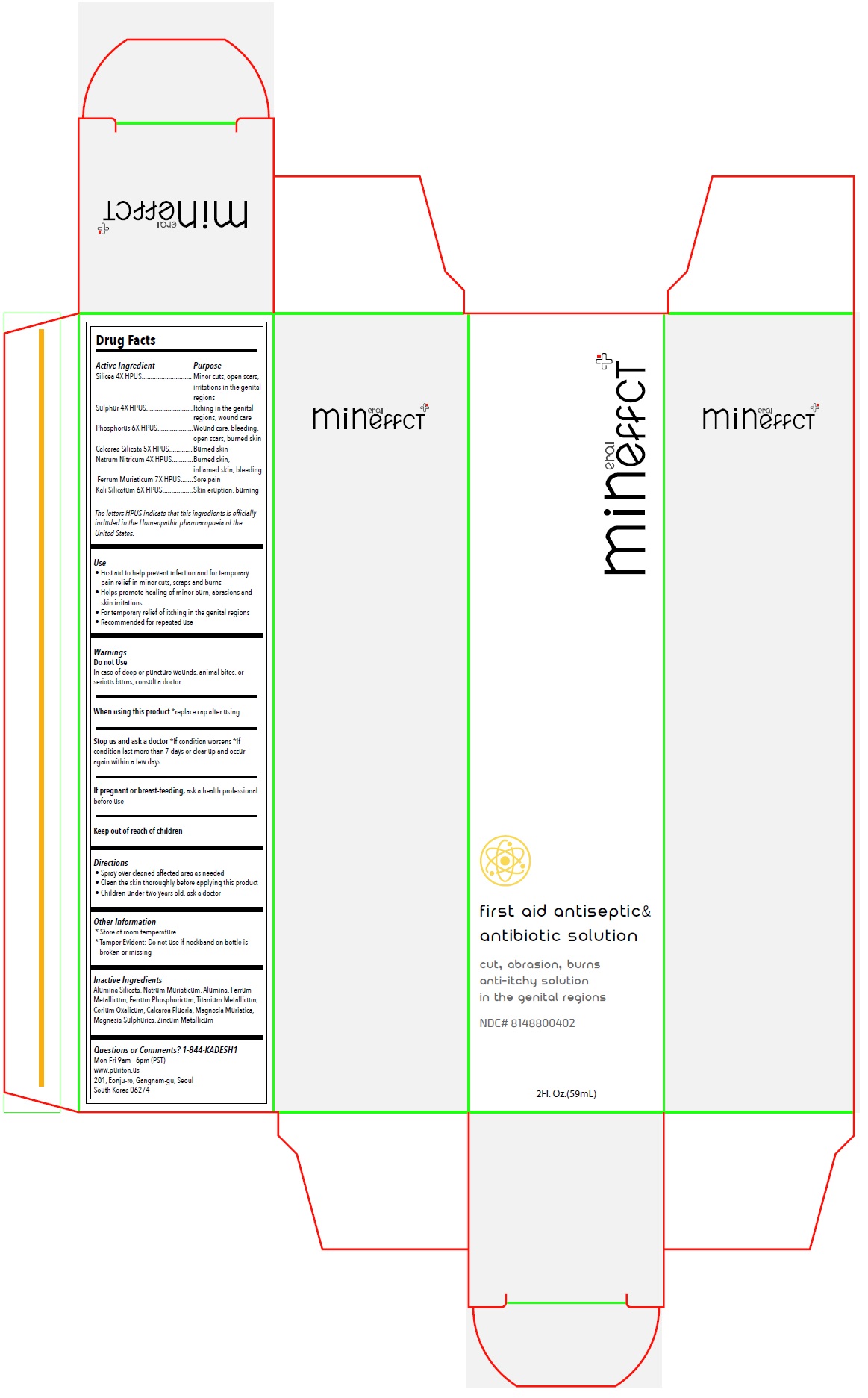 DRUG LABEL: Mineffect first aid antiseptic and antibiotic solution
NDC: 81488-004 | Form: SPRAY
Manufacturer: Kadesh Incoporation Co,Ltd
Category: homeopathic | Type: HUMAN OTC DRUG LABEL
Date: 20231031

ACTIVE INGREDIENTS: SILICON DIOXIDE 4 [hp_X]/59 mL; SULFUR 4 [hp_X]/59 mL; PHOSPHORUS 6 [hp_X]/59 mL; CALCIUM SILICATE 5 [hp_X]/59 mL; SODIUM NITRATE 4 [hp_X]/59 mL; FERRIC CHLORIDE HEXAHYDRATE 7 [hp_X]/59 mL; POTASSIUM SILICATE 6 [hp_X]/59 mL
INACTIVE INGREDIENTS: KAOLIN; SODIUM CHLORIDE; ALUMINUM OXIDE; IRON; FERROSOFERRIC PHOSPHATE; TITANIUM; CEROUS OXALATE NONAHYDRATE; CALCIUM FLUORIDE; MAGNESIUM CHLORIDE; MAGNESIUM SULFATE HEPTAHYDRATE; ZINC

Mineffect first aid antiseptic & antibiotic solution

Active Ingredient

Silicea 4X HPUS

Sulphur 4X HPUS

Phosphorus 6X HPUS

Calcarea Silicata 5X HPUS

Natrum Nitricum 4X HPUS

Ferrum Muriaticum 7X HPUS

Kali Silicatum 6X HPUS

The letters HPUS indicate that this ingredients is officially included in the Homeopathic pharmacopoeia of the United States.

Purpose

Minor cuts, open scars, irritations in the genital regions

Itching in the genital regions, wound care

Wound care, bleeding, open scars, burned skin

Burned skin

Burned skin, inflamed skin, bleeding

Sore pain

Skin eruption, burning

Use

• First aid to help prevent infection and for temporary pain relief in minor cuts, scrapes and burns

• Helps promote healing of minor burn, abrasions and skin irritations

• For temporary relief of itching in the genital regions

• Recommended for repeated use

Warnings

Do not Use

In case of deep or puncture wounds, animal bites, or serious burns, consult a doctor

When using this product*replace cap after using

Stop use and ask a doctor*If condition worsens *If condition last more than 7 days or clear up and occur again within a few days

If pregnant or breast-feeding,ask a health professional before use

Keep out of reach of children

Directions

• Spray over cleaned affected area as needed

• Clean the skin thoroughly before applying this product

• Children under two years old, ask a doctor

Other Information

* Store at room temperature

* Tamper Evident: Do not use if neckband on bottle is broken or missing

Inactive Ingredients

Alumina Silicata, Natrum Muriaticum, Alumina, Ferrum Metallicum, Ferrum Phosphoricum, Titanium Metallicum, Cerium Oxalicum, Calcarea Fluorica, Magnesia Muriatica, Magnesia Sulphurica, Zincum Metallicum

Questions or Comments? 1-844-KADESH1

Mon-Fri 9am - 6pm (PST)

www.puriton.us

201, Eonju-ro, Gangnam-gu, Seoul

South Korea 06274

cut, abrasion, burns anti-itchy solution in the genital regions